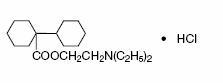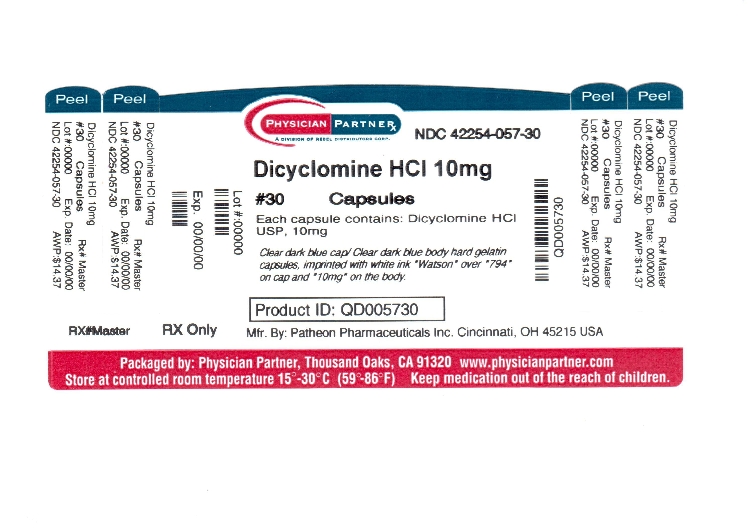 DRUG LABEL: Dicyclomine Hydrochloride
NDC: 42254-057 | Form: CAPSULE
Manufacturer: Rebel Distributors Corp
Category: prescription | Type: HUMAN PRESCRIPTION DRUG LABEL
Date: 20120620

ACTIVE INGREDIENTS: DICYCLOMINE HYDROCHLORIDE 10 mg/1 1
INACTIVE INGREDIENTS: D&C RED NO. 28; FD&C BLUE NO. 1; FD&C RED NO. 40; GELATIN; MAGNESIUM STEARATE; STARCH, CORN; SILICON DIOXIDE; SODIUM LAURYL SULFATE

70010341
Dicyclomine HCl
Capsules USP
Dicyclomine HCl
Tablets USP
Revised: May 2003
Rx only

DESCRIPTION

Dicyclomine hydrochloride is an antispasmodic and anticholinergic (antimuscarinic) agent. Dicyclomine hydrochloride occurs as a fine, white, crystalline, practically odorless powder with a bitter taste. It is soluble in water, freely soluble in alcohol and chloroform, and very slightly soluble in ether.

Chemically, it is [Bicyclohexyl]-1-carboxylic acid, 2-(diethyl-amino) ethyl ester, hydrochloride with the following structural formula:

C19H35NO2•HCI 345.95

Each capsule, for oral administration, contains 10 mg of dicyclomine hydrochloride.

Each tablet, for oral administration, contains 20 mg of dicyclomine hydrochloride.

This product contains the following inactive ingredients: colloidal silicon dioxide (tablets only), corn starch (tablets only), D&C red #28 (capsules only), FD&C blue #1 (capsules only), FD&C blue #1 lake (tablets only), FD&C red #40 (capsules only), gelatin (capsules only), hypromellose (tablets only), lactose monohydrate (tablets only), magnesium stearate (capsules only), pregelatinized starch, silicon dioxide (capsules only), sodium lauryl sulfate (capsules only), sodium starch glycolate (tablets only), and stearic acid (tablets only).

CLINICAL PHARMACOLOGY

Dicyclomine relieves smooth muscle spasm of the gastrointestinal tract. Animal studies indicate that this action is achieved via a dual mechanism: (1) a specific anticholinergic effect (antimuscarinic) at the acetylcholine- receptor sites with approximately 1/8 the milligram potency of atropine (in vitro, guinea pig ileum); and (2) a direct effect upon smooth muscle (musculotropic) as evidenced by dicyclomine's antagonism of bradykinin- and histamine-induced spasms of the isolated guinea pig ileum. Atropine did not affect responses to these two agonists. In vivo studies in cats and dogs showed dicyclomine to be equally potent against acetylcholine (ACh)- or barium chloride (BaCI2)- induced intestinal spasm while atropine was at least 200 times more potent against effects of ACh than BaCI2. Tests for mydriatic effects in mice showed that dicyclomine was approximately 1/500 as potent as atropine; antisialogogue tests in rabbits showed dicyclomine to be 1/300 as potent as atropine.

In man, dicyclomine is rapidly absorbed after oral administration, reaching peak values within 60-90 minutes. The principal route of elimination is via the urine (79.5% of the dose). Excretion also occurs in the feces, but to a lesser extent (8.4%). Mean half-life of plasma elimination in one study was determined to be approximately 1.8 hours when plasma concentrations were measured for 9 hours after a single dose. In subsequent studies, plasma concentrations were followed for up to 24 hours after a single dose, showing a secondary phase of elimination with a somewhat longer half-life. Mean volume of distribution for a 20 mg oral dose is approximately 3.65 L/kg suggesting extensive distribution in tissues.

In controlled clinical trials involving over 100 patients who received drug, 82% of patients treated for functional bowel/irritable bowel syndrome with dicyclomine hydrochloride at initial doses of 160 mg daily (40 mg q.i.d.) demonstrated a favorable clinical response compared with 55% treated with placebo (p<.05). In these trials, most of the side effects were typically anticholinergic in nature (see table) and were reported by 61% of the patients.

 | Dicyclomine
 | Hydrochloride
 | (40 mg q.i.d.) | Placebo
Side Effect | % | %
Dry Mouth | 33 | 5
Dizziness | 29 | 2
Blurred Vision | 27 | 2
Nausea | 14 | 6
Light-headedness | 11 | 3
Drowsiness | 9 | 1
Weakness | 7 | 1
Nervousness | 6 | 2

Nine percent (9%) of patients were discontinued from the drug because of one or more of these side effects (compared with 2% in the placebo group). In 41% of the patients with side effects, side effects disappeared or were tolerated at the 160 mg daily dose without reduction. A dose reduction from 160 mg daily to an average daily dose of 90 mg was required in 46% of the patients with side effects who then continued to experience a favorable clinical response; their side effects either disappeared or were tolerated. (See ADVERSE REACTIONS.)

INDICATIONS AND USAGE

For the treatment of functional bowel/irritable bowel syndrome.

CONTRAINDICATIONS

Obstructive uropathy
Obstructive disease of the gastrointestinal tract
Severe ulcerative colitis (See PRECAUTIONS)
Reflux esophagitis
Unstable cardiovascular status in acute hemorrhage
Glaucoma
Myasthenia gravis
Evidence of prior hypersensitivity to dicyclomine hydrochloride or other ingredients of these formulations
Infants less than 6 months of age (See WARNINGS and PRECAUTIONS: Information for Patients.)
Nursing Mothers (See WARNINGS and PRECAUTIONS: Information for Patients).

WARNINGS

In the presence of a high environmental temperature, heat prostration can occur with drug use (fever and heat stroke due to decreased sweating). If symptoms occur, the drug should be discontinued and supportive measures instituted.

Diarrhea may be an early symptom of incomplete intestinal obstruction, especially in patients with ileostomy or colostomy. In this instance, treatment with this drug would be inappropriate and possibly harmful.

Dicyclomine may produce drowsiness or blurred vision. The patient should be warned not to engage in activities requiring mental alertness, such as operating a motor vehicle or other machinery or performing hazardous work while taking this drug.

Psychosis has been reported in sensitive individuals given anticholinergic drugs. CNS signs and symptoms include confusion, disorientation, short-term memory loss, hallucinations, dysarthria, ataxia, coma, euphoria, decreased anxiety, fatigue, insomnia, agitation and mannerisms, and inappropriate affect. These CNS signs and symptoms usually resolve within 12 to 24 hours after discontinuation of the drug.

There are reports that administration of dicyclomine syrup to infants has been followed by serious respiratory symptoms (dyspnea, shortness of breath, breathlessness, respiratory collapse, apnea, asphyxia), seizures, syncope, pulse rate fluctuations, muscular hypotonia, and coma. Death has been reported. No causal relationship between these effects observed in infants and dicyclomine administration has been established. DICYCLOMINE IS CONTRAINDICATED IN INFANTS LESS THAN 6 MONTHS OF AGE AND IN NURSING MOTHERS. (See CONTRAINDICATIONS, and PRECAUTIONS: Nursing Mothers and Pediatric Use).

Safety and efficacy of dicyclomine hydrochloride in pediatric patients have not been established.

PRECAUTIONS

General

Use with caution in patients with:

Autonomic neuropathy
Hepatic or renal disease
Ulcerative colitis—large doses may suppress intestinal motility to the point of producing a paralytic ileus and the use of this drug may precipitate or aggravate the serious complication of toxic megacolon (see CONTRAINDICATIONS)
Hyperthyroidism
Hypertension
Coronary heart disease
Congestive heart failure
Cardiac tachyarrhythmia
Hiatal hernia (see CONTRAINDICATIONS: reflux esophagitis)
Known or suspected prostatic hypertrophy.

Investigate any tachycardia before administration of dicyclomine hydrochloride, since it may increase the heart rate.

With overdosage, a curare-like action may occur (i.e., neuromuscular blockade leading to muscular weakness and possible paralysis).

Information For Patients

Dicyclomine may produce drowsiness or blurred vision. The patient should be warned not to engage in activities requiring mental alertness, such as operating a motor vehicle or other machinery or to perform hazardous work while taking this drug.

Dicyclomine is contraindicated in infants less than 6 months of age and in nursing mothers. (See CONTRAINDICATIONS, WARNINGS, and PRECAUTlONS: Nursing Mothers and Pediatric Use).

In the presence of a high environmental temperature, heat prostration can occur with drug use (fever and heat stroke due to decreased sweating).

If symptoms occur, the drug should be discontinued and a physician contacted.

Drug Interactions

The following agents may increase certain actions or side effects of anticholinergic drugs: amantadine, antiarrhythmic agents of Class I (e.g., quinidine), antihistamines, antipsychotic agents (e.g., phenothiazines), benzodiazepines, MAO inhibitors, narcotic analgesics (e.g., meperidine), nitrates and nitrites, sympathomimetic agents, tricyclic antidepressants, and other drugs having anticholinergic activity.

Anticholinergics antagonize the effects of antiglaucoma agents. Anticholinergic drugs in the presence of increased intraocular pressure may be hazardous when taken concurrently with agents such as corticosteroids. (See also CONTRAINDICATIONS.)

Anticholinergic agents may affect gastrointestinal absorption of various drugs, such as slowly dissolving dosage forms of digoxin; increased serum digoxin concentrations may result. Anticholinergic drugs may antagonize the effects of the drugs that alter gastrointestinal motility, such as metoclopramide. Because antacids may interfere with the absorption of anticholinergic agents, simultaneous use of these drugs should be avoided.

The inhibiting effects of anticholinergic drugs on gastric hydrochloric acid secretion are antagonized by agents used to treat achlorhydria and those used to test gastric secretion.

Carcinogenesis, Mutagenesis, Impairment of Fertility

There are no known human data on long-term potential for carcinogenicity or mutagenicity.

Long-term studies in animals to determine carcinogenic potential are not known to have been conducted.

In studies in rats at doses of up to 100 mg/kg/day, dicyclomine produced no deleterious effects on breeding, conception, or parturition.

Pregnancy

Teratogenic Effects

Pregnancy Category B.

Reproduction studies have been performed in rats and rabbits at doses up to 33 times the maximum recommended human dose based on 160 mg/day (3 mg/kg) and have revealed no evidence of impaired fertility or harm to the fetus due to dicyclomine. Epidemiologic studies in pregnant women with products containing dicyclomine hydrochloride (at doses up to 40 mg/day) have not shown that dicyclomine increases the risk of fetal abnormalities if administered during the first trimester of pregnancy. There are, however, no adequate and well-controlled studies in pregnant women at the recommended doses (80-160 mg/day). Because animal reproduction studies are not always predictive of human response, dicyclomine as indicated for functional bowel/irritable bowel syndrome should be used during pregnancy only if clearly needed.

Nursing Mothers

Since dicyclomine has been reported to be excreted in human milk, DICYCLOMINE HYDROCHLORIDE IS CONTRAINDICATED IN NURSING MOTHERS. (See CONTRAINDICATIONS, WARNINGS, PRECAUTIONS: Pediatric Use, and ADVERSE REACTIONS).

Pediatric Use

(See CONTRAINDICATIONS, WARNINGS, and PRECAUTIONS: Nursing Mothers.) DICYCLOMINE IS CONTRAINDICATED IN INFANTS LESS THAN 6 MONTHS OF AGE.

Safety and effectiveness in pediatric patients have not been established.

ADVERSE REACTIONS

Controlled clinical trials have provided frequency information for reported adverse effects of dicyclomine hydrochloride listed in a decreasing order of frequency. (See CLINICAL PHARMACOLOGY.)

Not all of the following adverse reactions have been reported with dicyclomine hydrochloride. Adverse reactions are included here that have been reported for pharmacologically similar drugs with anticholinergic/antispasmodic action.

Gastrointestinal: dry mouth, nausea, vomiting, constipation, bloated feeling, abdominal pain, taste loss, anorexia
Central Nervous System: dizziness, light-headedness, tingling, headache, drowsiness, weakness, nervousness, numbness, mental confusion and/or excitement (especially in elderly persons), dyskinesia, lethargy, syncope, speech disturbance, insomnia
Ophthalmologic: blurred vision, diplopia, mydriasis, cycloplegia, increased ocular tension
Dermatological/Allergic: rash, urticaria, itching, and other dermal manifestations; severe allergic reaction or drug idiosyncrasies including anaphylaxis
Genitourinary: urinary hesitancy, urinary retention
Cardiovascular: tachycardia, palpitations
Respiratory: Dyspnea, apnea, asphyxia (see WARNINGS)
Other: decreased sweating, nasal stuffiness or congestion, sneezing, throat congestion, impotence, suppression of lactation (see PRECAUTlONS: Nursing Mothers)

DRUG ABUSE AND DEPENDENCE

Abuse of and/or dependence on dicyclomine for anticholinergic effects have been rarely reported.

OVERDOSAGE

Signs and Symptoms

The signs and symptoms of overdosage are headache; nausea; vomiting; blurred vision; dilated pupils; hot, dry skin; dizziness; dryness of the mouth; difficulty in swallowing; and CNS stimulation. A curare-like action may occur (i.e., neuromuscular blockade leading to muscular weakness and possible paralysis).

A 37-year-old female reported numbness on the left side, cold fingertips, blurred vision, abdominal and flank pain, decreased appetite, dry mouth, and nervousness following ingestion of 320 mg daily (four 20 mg tablets QID) for four days. These events resolved after discontinuing the dicyclomine.

Oral LD50

The acute oral LD50 of the drug is 625 mg/kg in mice.

Minimum Human Lethal Dose/Maximum Human Dose Recorded

The amount of drug in a single dose that is ordinarily associated with symptoms of overdosage or that is Iikely to be life threatening, has not been defined. The maximum human oral dose recorded was 600 mg by mouth in a 10-month-old child and approximately 1500 mg in an adult, each of whom survived.

In three of the infants who died following administration of dicyclomine hydrochloride (see WARNINGS), the blood concentrations of drug were 200, 220, and 505 ng/mL, respectively.

Dialysis

It is not known if dicyclomine is dialyzable.

Treatment

Treatment should consist of gastric lavage, emetics, and activated charcoal. Sedatives (e.g., short-acting barbiturates, benzodiazepines) may be used for management of overt signs of excitement. If indicated, an appropriate parenteral cholinergic agent may be used as an antidote.

DOSAGE AND ADMINISTRATION

DOSAGE MUST BE ADJUSTED TO INDIVIDUAL PATIENT NEEDS. (See CLINICAL PHARMACOLOGY.)

The only oral dose clearly shown to be effective is 160 mg per day (in 4 equally divided doses). Since this dose is associated with a significant incidence of side effects, it is prudent to begin with 80 mg per day (in 4 equally divided doses). Depending upon the patient's response during the first week of therapy, the dose should be increased to 160 mg per day unless side effects limit dosage escalation.

If efficacy is not achieved within 2 weeks or side effects require doses below 80 mg per day, the drug should be discontinued. Documented safety data are not available for doses above 80 mg daily for periods longer than 2 weeks.

The intramuscular dosage form is to be used temporarily when the patient cannot take oral medication. Intramuscular injection is about twice as bioavailable as oral dosage forms; consequently, the recommended intramuscular dose is 80 mg daily (in 4 equally divided doses).

Oral dicyclomine hydrochloride should be started as soon as possible and the intramuscular form should not be used for periods longer than 1 or 2 days.

HOW SUPPLIED

Dicyclomine Hydrochloride Capsules USP and Dicyclomine Hydrochloride Tablets USP are supplied as follows:

10 mg capsules: Clear Dark Blue cap/Clear Dark Blue body hard gelatin capsules, imprinted with white ink WATSON over 794 on cap and 10 mg on the body, in bottles of 30 and 90.

Storage

Store at controlled room temperature 15°-30°C (59°-86°F).

Dispense in a well-closed container as defined in USP/NF.

Manufactured for:
Watson Laboratories, Inc.
Corona, CA 92880 USA

Manufactured by:
Patheon Pharmaceuticals Inc.
Cincinnati, OH 45215 USA

Repackaged by:
Rebel Distributors Corp.
Thousand Oaks, CA 91320